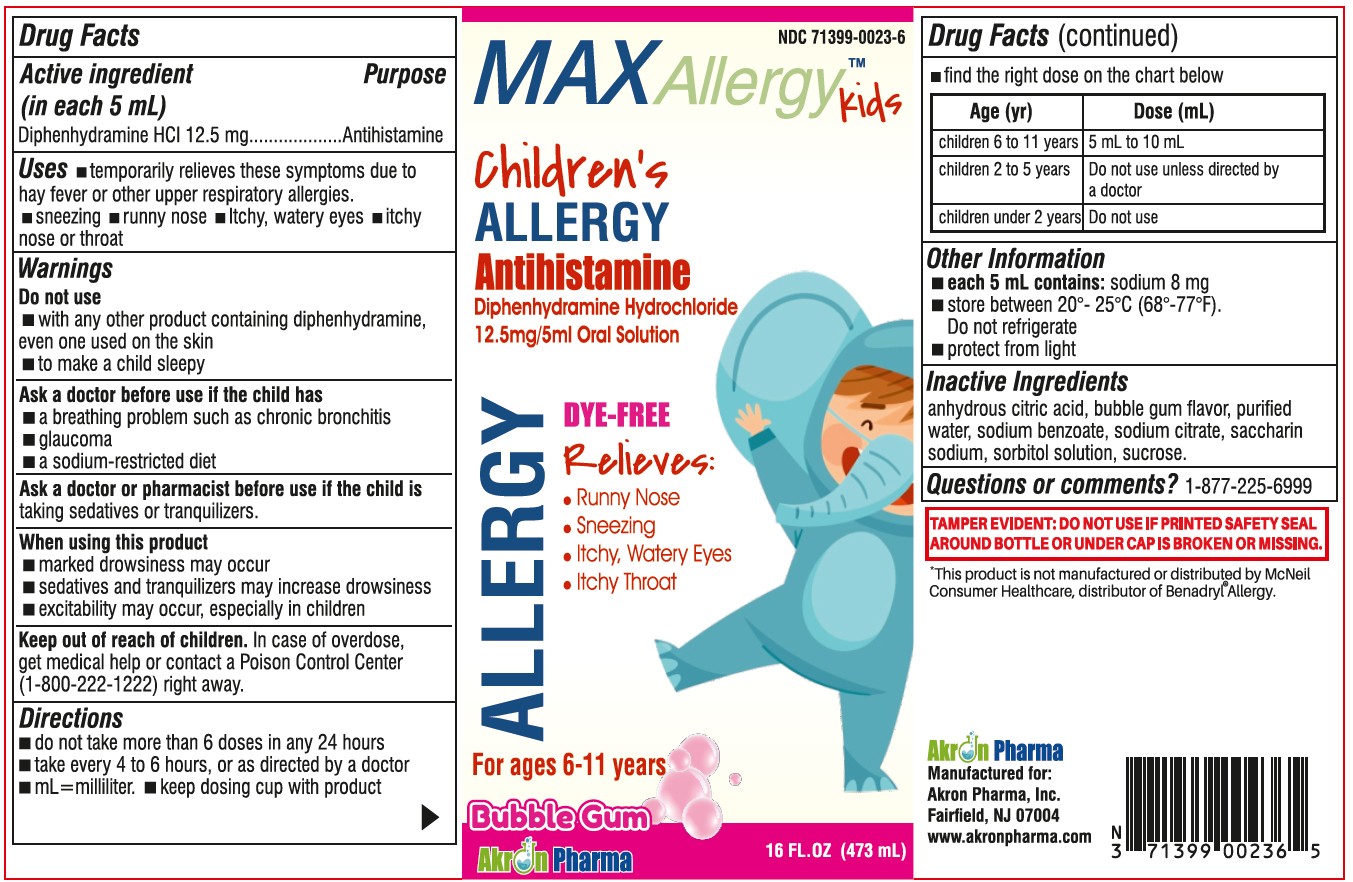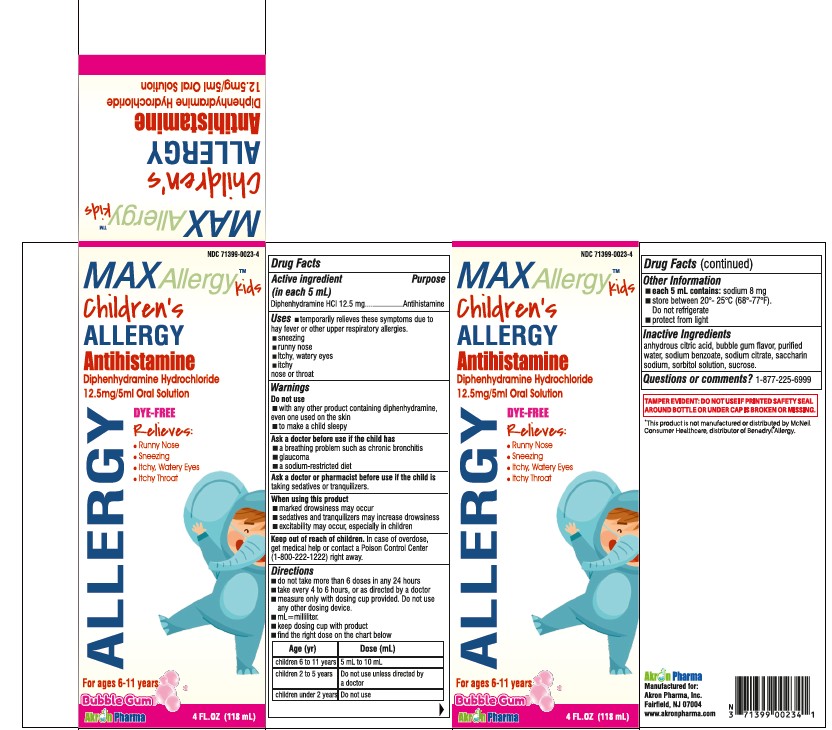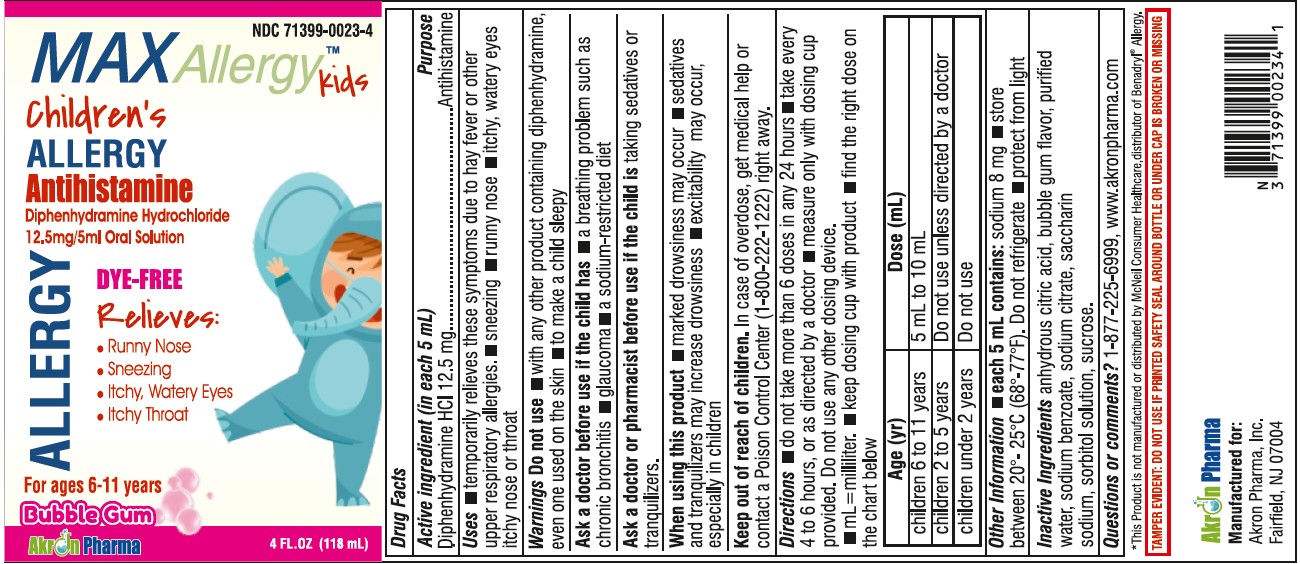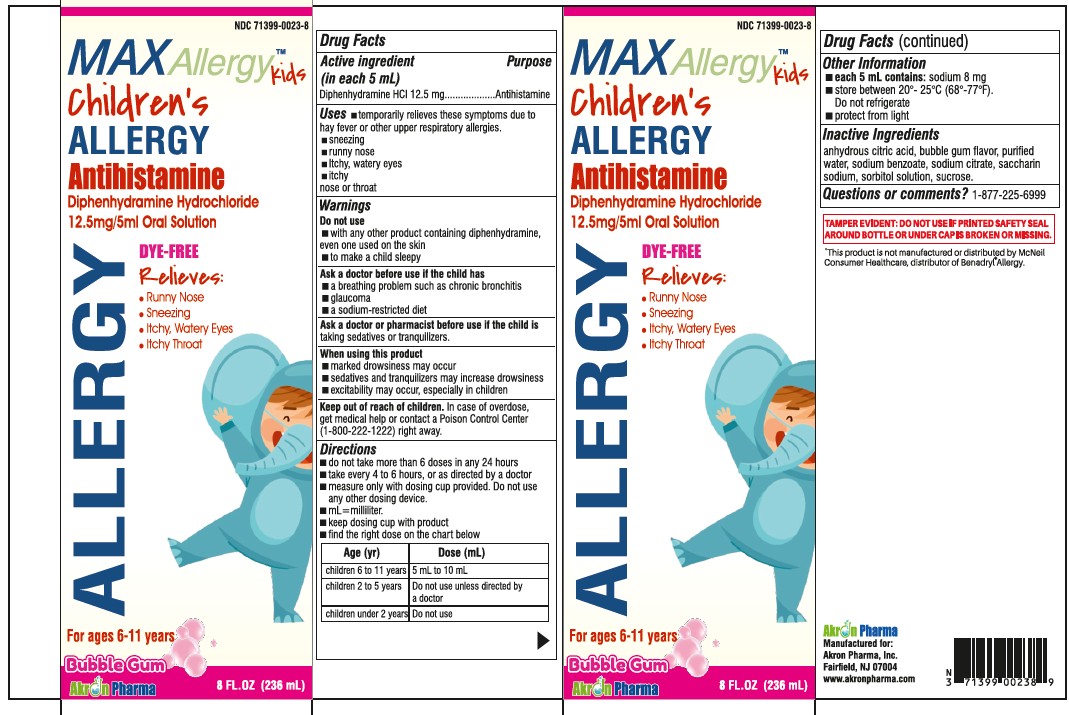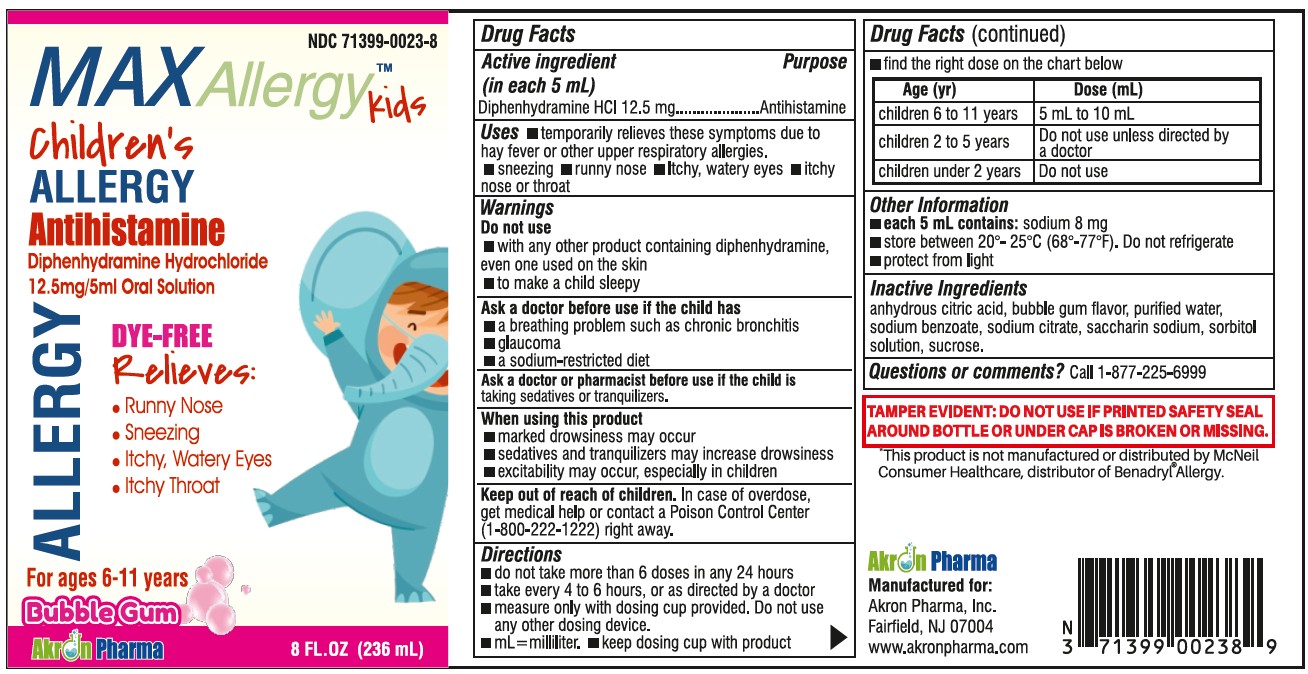 DRUG LABEL: MAX ALLERGY KIDS
NDC: 71399-0023 | Form: SOLUTION
Manufacturer: Akron Pharma Inc.
Category: otc | Type: HUMAN OTC DRUG LABEL
Date: 20251027

ACTIVE INGREDIENTS: DIPHENHYDRAMINE HYDROCHLORIDE 12.5 mg/5 mL
INACTIVE INGREDIENTS: ANHYDROUS CITRIC ACID; WATER; SODIUM BENZOATE; SODIUM CITRATE; SACCHARIN SODIUM; SORBITOL; SUCROSE

MAX Allergy Kids
Childrens Allergy
Antihistamine
Diphenhydramine Hydrochloride
12.5mg/5ml Orol Solution
DYE-FREE

Active ingredient (in each 5 mL)

Diphenhydramine HCl 12.5 mg

Purpose

Antihistamine

Uses

- temporarily relieves these symptoms due to hay fever or other upper respiratory allergies:
  - sneezing
  - runny nose
  - itchy, watery eyes
  - itchy of the nose or throat

Warnings

Do not use

- with any other product containing diphenhydramine, even one used on skin
- to make a child sleepy

Ask a doctor before use if the child has

- a breathing problem such as chronic bronchitis
- glaucoma
- a sodium restricted diet

Ask a doctor or pharmacist before use if the child is

taking sedatives or tranquilizers.

When using this product

- marked drowsiness may occur
- sedatives and tranquilizers may increase drowsiness
- excitabillty may occur, especially in children

Keep out of reach of children.

In case of overdose, get medical help or contact a Poison Control Center (1-800-222-1222) right away.

Directions

- do not take more than 6 doses in any 24 hours
- take every 4 to 6 hours, or as directed by a doctor
- measure only with dosing cup provided. Do not use any other dosing device.
- mL = milliliter
- keep dosing cup with product
- find the right dose on the chart below

Age (yr) | Dose (mL)
children 6 to 11 years | 5 mL to 10 mL
children 2 to 5 years | Do not use unless directed by a doctor
children under 2 years | Do not use

Other information

- each 5 mL contains:sodium 8 mg
- store between 20°- 25°C (68°-77°F). Do not refrigerate
- protect from light

Inactive ingredients

anhydrous citric acid, bubble gum flavor, purified water, sodium benzoate, sodium citrate, saccharin sodium, sorbitol solution, sucrose.

Questions or comments?

Please Call 1(877) 225-6999

Manufactured for:
Akron Pharma, Inc,
Fairfield, NJ 07004
Manufactured in U.S.A